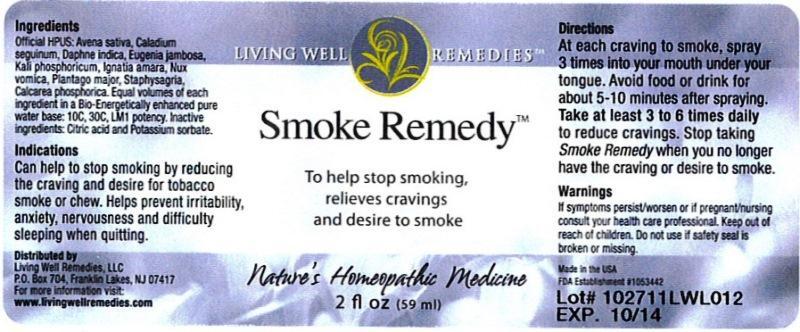 DRUG LABEL: Smoke Remedy
NDC: 53852-0001 | Form: LIQUID
Manufacturer: Living Well Remedies, LLC
Category: homeopathic | Type: HUMAN OTC DRUG LABEL
Date: 20141031

ACTIVE INGREDIENTS: AVENA SATIVA FLOWERING TOP 10 [hp_C]/59 mL; DIEFFENBACHIA SEGUINE 10 [hp_C]/59 mL; TRIBASIC CALCIUM PHOSPHATE 10 [hp_C]/59 mL; DAPHNE ODORA BARK 10 [hp_C]/59 mL; SYZYGIUM JAMBOS SEED 10 [hp_C]/59 mL; STRYCHNOS IGNATII SEED 10 [hp_C]/59 mL; POTASSIUM PHOSPHATE, DIBASIC 10 [hp_C]/59 mL; STRYCHNOS NUX-VOMICA SEED 10 [hp_C]/59 mL; PLANTAGO MAJOR 10 [hp_C]/59 mL; DELPHINIUM STAPHISAGRIA SEED 10 [hp_C]/59 mL
INACTIVE INGREDIENTS: CITRIC ACID MONOHYDRATE; POTASSIUM SORBATE; WATER

Smoke Remedy

DOSAGE AND ADMINISTRATION

Directions: At each craving to smoke, spray 3 times into your mouth under your tongue. Avoid food or drink for about 5-10 minutes after spraying. Take at least 3 to 6 times daily to reduce cravings. Stop taking Smoke Remedy when you no longer have the craving or desire to smoke.

WARNINGS

Warnings: If symptoms persist/worsen or if pregnant/nursing, consult a health care professional.

Keep out of reach of children.

OTHER SAFETY INFORMATION

Other: Do not use if safety seal is broken or missing.

PURPOSE

Uses: Can help to stop smoking by reducing the craving and desire for tobacco smoke or chew. Helps prevent irritability, anxiety, nervousness and difficulty sleeping when quitting.

ACTIVE INGREDIENT

Ingredients: Official HPUS: Avena sativa, Caladium seguinum, Calcarea phosphorica, Daphne indica, Eugenia jambosa, Ignatia amara, Kali phosphoricum, Nux vomica, Plantago major, Staphysagria. Equal volumes of each ingredient in 10C, 30C, LM1 potencies.

INACTIVE INGREDIENT

Inactive ingredients: Bio-Energetically enhanced pure water, citric acid, potassium sorbate.

Uses:

- Can help to stop smoking by reducing the craving and desire for tobacco smoke or chew.
- Helps prevent irritability, anxiety, nervousness and difficulty sleeping when quitting.